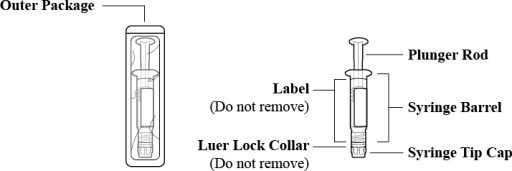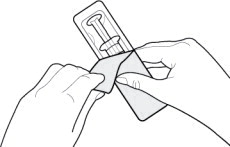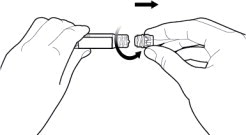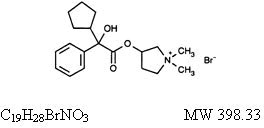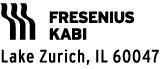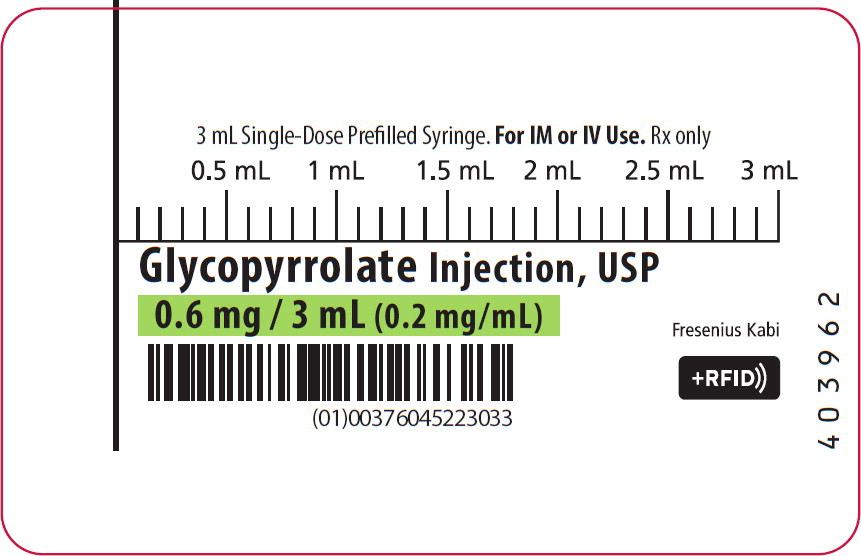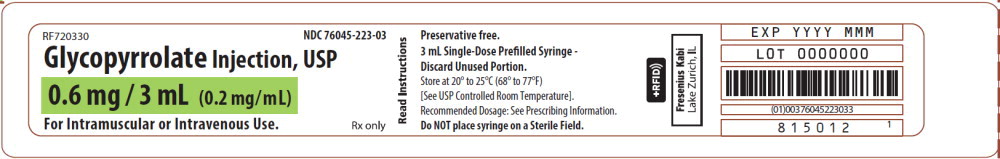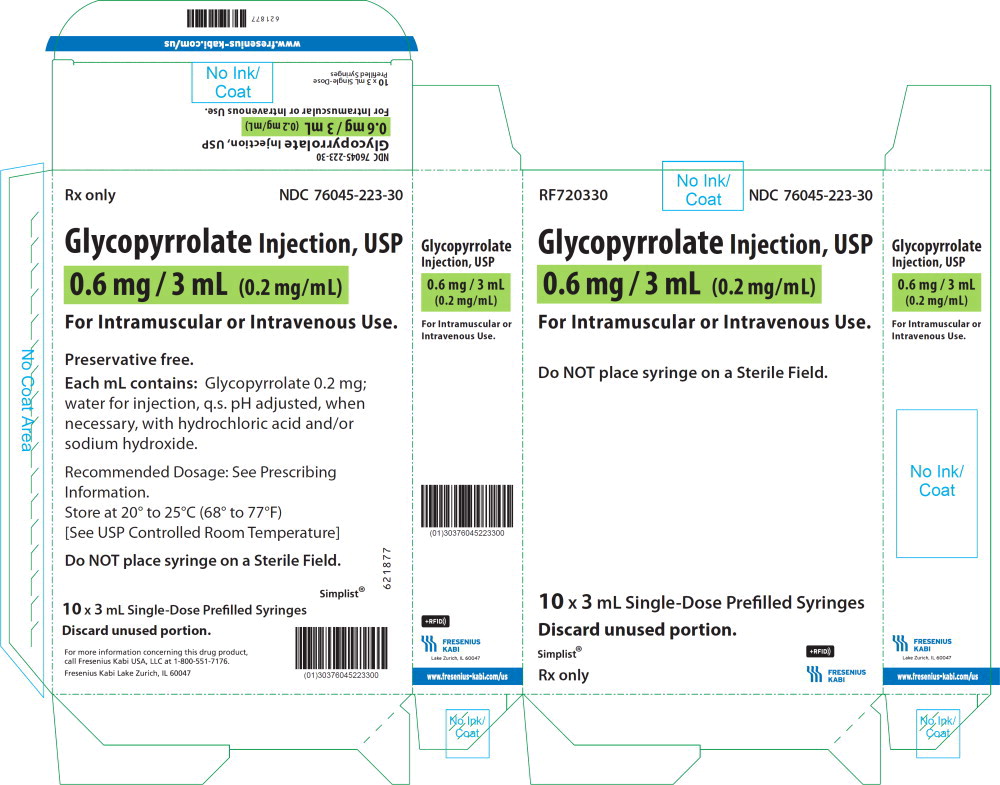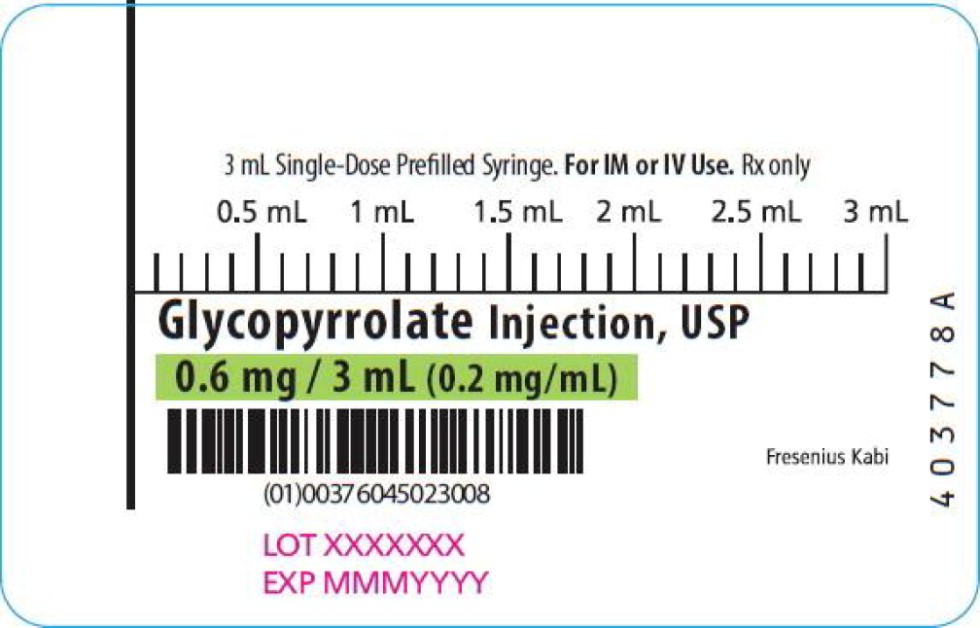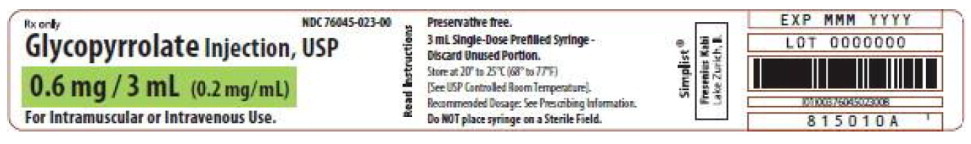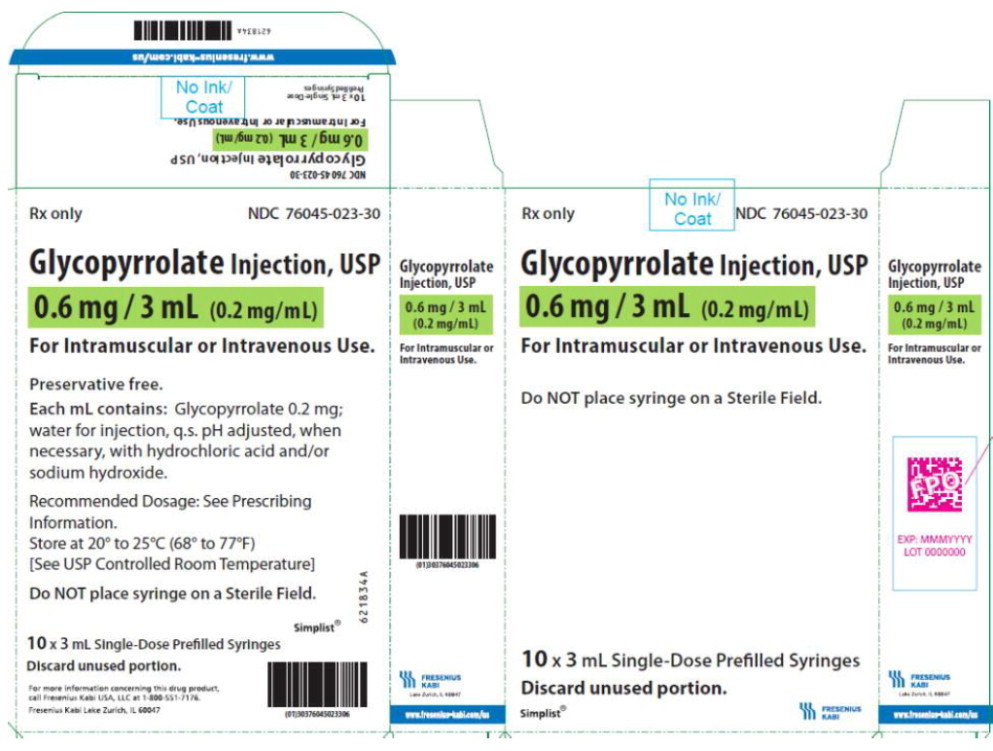 DRUG LABEL: Glycopyrrolate

NDC: 76045-023 | Form: INJECTION
Manufacturer: Fresenius Kabi USA, LLC
Category: prescription | Type: HUMAN PRESCRIPTION DRUG LABEL
Date: 20240514

ACTIVE INGREDIENTS: GLYCOPYRROLATE
 0.2 mg/1 mL
INACTIVE INGREDIENTS: WATER; HYDROCHLORIC ACID; SODIUM HYDROXIDE

HIGHLIGHTS OF PRESCRIBING INFORMATION

These highlights do not include all the information needed to use GLYCOPYRROLATE INJECTION safely and effectively. See full prescribing information for GLYCOPYRROLATE INJECTION.
GLYCOPYRROLATE injection, for intramuscular or intravenous use
Initial U.S. Approval: 1961

1 INDICATIONS AND USAGE

Glycopyrrolate Injection is an anticholinergic indicated:

in anesthesia (adult and pediatric patients)

- for reduction of airway or gastric secretions, and volume and acidity of gastric secretions, and blockade of cardiac inhibitory reflexes during induction of anesthesia and intubation,
- intraoperatively to counteract surgically or drug-induced or vagal reflex-associated arrhythmias, and
- for protection against peripheral muscarinic effects of cholinergic agents. (1)

in peptic ulcer (adults)

- as adjunctive therapy for the treatment of peptic ulcer when rapid anticholinergic effect is desired or oral medication is not tolerated.

2 DOSAGE AND ADMINISTRATION

Glycopyrrolate Injection may be administered intramuscularly, or intravenously, without dilution, in the following indications:

Adults (2.2)

Preanesthetic Medication: 0.004 mg/kg IM, given 30 to 60 minutes prior to the anticipated time of induction of anesthesia

Intraoperative Medication: single doses of 0.1 mg IV and repeated, as needed, at intervals of 2 to 3 minutes

Reversal of Neuromuscular Blockade: 0.2 mg for each 1 mg of neostigmine or 5 mg of pyridostigmine

Peptic Ulcer: 0.1 mg IV or IM at 4-hour intervals, 3 or 4 times daily

Pediatric patients (2.3)

Preanesthetic Medication: 0.004 mg/kg IM, given 30 to 60 minutes prior to the anticipated time of induction of anesthesia. Patients under 2 years of age may require up to 0.009 mg/kg

Intraoperative Medication: 0.004 mg/kg IV, not to exceed 0.1 mg in a single dose and repeated, as needed, at intervals of 2 to 3 minutes

Reversal of Neuromuscular Blockade: 0.2 mg for each 1 mg of neostigmine or 5 mg of pyridostigmine

Peptic Ulcer: Glycopyrrolate Injection is not indicated for the treatment of peptic ulcer in pediatric patients

Do not use prefilled syringe to administer a dose of less than 0.1 mg (0.5 mL). (2.3)

See Full Prescribing Information for preparation, handling, and instructions for use of pre-filled syringe (2.4, 2.5)

3 DOSAGE FORMS AND STRENGTHS

Injection: 0.6 mg/3 mL (0.2 mg/mL) prefilled, single-dose, disposable syringes. (3)

4 CONTRAINDICATIONS

- Known hypersensitivity to glycopyrrolate or any of its inactive ingredients. (4)
- Peptic ulcer patients with glaucoma; obstructive uropathy; obstructive disease of the gastrointestinal tract; paralytic ileus, intestinal atony of the elderly or debilitated patient; unstable cardiovascular status in acute hemorrhage; severe ulcerative colitis; toxic megacolon; complicating ulcerative colitis; myasthenia gravis. (4)

5 WARNINGS AND PRECAUTIONS

- Precipitation of Acute Glaucoma: Glycopyrrolate Injection may cause mydriasis and increase intraocular pressure in patients with glaucoma. Advise patients with glaucoma to promptly seek medical care if they experience symptoms of acute angle closure glaucoma. (5.1)
- Drowsiness or Blurred Vision: May cause drowsiness or blurred vision. Advise patients not to drive or perform hazardous work until resolved. (5.2)
- Heat Prostration: Advise patients to avoid exertion and high environmental temperatures after receiving Glycopyrrolate Injection. (5.3)
- Intestinal Obstruction: Diarrhea may be an early symptom of incomplete intestinal obstruction. Avoid use in patients with diarrhea and ileostomy or colostomy. (5.4)
- Tachycardia: Increase in heart rate may occur. Use with caution in patients with coronary artery disease, congestive heart failure, cardiac arrhythmias, hypertension, or hyperthyroidism. (5.5)

6 ADVERSE REACTIONS

Most common adverse reactions are related to anticholinergic pharmacology and may include xerostomia (dry mouth); urinary hesitancy and retention; blurred vision and photophobia due to mydriasis (dilation of the pupil); cycloplegia; increased ocular tension; tachycardia; bradycardia; palpitation; and decreased sweating. (6)

To report SUSPECTED ADVERSE REACTIONS, contact Fresenius Kabi USA, LLC at 1-800-551-7176 or FDA at 1-800-FDA-1088 or www.fda.gov/medwatch.

7 DRUG INTERACTIONS

- Other anticholinergics or drugs with anticholinergic activity: May intensify the antimuscarinic effects and result in an increase in anticholinergic side effects. (7)
- Potassium Chloride in a Wax Matrix: May increase severity of potassium chloride-induced gastrointestinal lesions. (7)

8 USE IN SPECIFIC POPULATIONS

- Pediatric Use: Infants, patients with Down's Syndrome, and pediatric patients with spastic paralysis or brain damage may experience an increased response to anticholinergics, thus increasing the potential for side effects. Large doses may cause hyperexcitability. (8.4)

FULL PRESCRIBING INFORMATION

1 INDICATIONS AND USAGE

Glycopyrrolate Injection, USP (0.2 mg/mL) is an anticholinergic indicated for use in:

anesthesia (all ages)

- for reduction of salivary, tracheobronchial, and pharyngeal secretions, reduction of volume and acidity of gastric secretions, and blockade of cardiac inhibitory reflexes during induction of anesthesia and intubation,
- intraoperatively to counteract surgically or drug-induced or vagal reflex-associated arrhythmias, and
- for protection against peripheral muscarinic effects of cholinergic agents such as neostigmine and pyridostigmine given to reverse the neuromuscular blockade due to non-depolarizing agents.

peptic ulcer (adults)

- as adjunctive therapy for the treatment of peptic ulcer when rapid anticholinergic effect is desired or when oral medication is not tolerated.

2 DOSAGE AND ADMINISTRATION

2.1 General Dosing and Administration Information

- Parenteral drug products should be inspected visually for particulate matter and discoloration prior to administration whenever solution and container permit.
- Glycopyrrolate Injection may be administered intramuscularly, or intravenously, without dilution.
- Do not introduce any other fluid into the syringe at any time.
- Do not dilute for IV push.
- Do not re-sterilize the syringe.
- Do not use this product on a sterile field.
- This product is for single dose only.

2.2 Dosing in Adults

Preanesthetic Medication

The recommended dose of Glycopyrrolate Injection is 0.004 mg/kg by intramuscular injection, given 30 to 60 minutes prior to the anticipated time of induction of anesthesia or at the time the preanesthetic narcotic and/or sedative are administered.

Intraoperative Medication

Glycopyrrolate Injection may be used during surgery to counteract drug-induced or vagal reflexes and their associated arrhythmias (e.g., bradycardia). It should be administered intravenously as single doses of 0.1 mg and repeated, as needed, at intervals of 2 to 3 minutes. Attempt to determine the etiology of the arrhythmia, and perform the surgical or anesthetic manipulations necessary to correct parasympathetic imbalance.

Reversal of Neuromuscular Blockade

The recommended dose of Glycopyrrolate Injection is 0.2 mg for each 1 mg of neostigmine or 5 mg of pyridostigmine.

Peptic Ulcer

The usual recommended dose of Glycopyrrolate Injection is 0.1 mg administered at 4-hour intervals, 3 or 4 times daily intravenously or intramuscularly. Where more profound effect is required, 0.2 mg may be given. Some patients may need only a single dose. Frequency of administration should be dictated by patient response up to a maximum of four times daily.

2.3 Dosing in Pediatric Patients

Preanesthetic Medication

The recommended dose of Glycopyrrolate Injection in pediatric patients is 0.004 mg/kg intramuscularly, given 30 to 60 minutes prior to the anticipated time of induction of anesthesia or at the time the preanesthetic narcotic and/or sedative are administered. Patients under 2 years of age may require up to 0.009 mg/kg.

Do not use this prefilled syringe to administer a dose of less than 0.1 mg (0.5 mL).

Intraoperative Medication

Because of the long duration of action of Glycopyrrolate Injection if used as preanesthetic medication, additional Glycopyrrolate Injection for anticholinergic effect intraoperatively is rarely needed; in the event it is required the recommended pediatric dose is 0.004 mg/kg intravenously, not to exceed 0.1 mg in a single dose which may be repeated, as needed, at intervals of 2 to 3 minutes. Attempt to determine the etiology of the arrhythmia, and perform the surgical or anesthetic manipulations necessary to correct parasympathetic imbalance.

Do not use this prefilled syringe to administer a dose of less than 0.1 mg (0.5 mL).

Reversal of Neuromuscular Blockade

The recommended pediatric dose of Glycopyrrolate Injection is 0.2 mg for each 1 mg of neostigmine or 5 mg of pyridostigmine. In order to minimize the appearance of cardiac side effects, the drugs may be administered simultaneously by intravenous injection and may be mixed in the same syringe.

Do not use this prefilled syringe to administer a dose of less than 0.1 mg (0.5 mL).

Peptic Ulcer

Glycopyrrolate Injection is not indicated for the treatment of peptic ulcer in pediatric patients.

2.4 Preparation and Handling

Diluent Compatibilities

Dextrose 5% and 10% in water, or saline, dextrose 5% in sodium chloride 0.45%, sodium chloride 0.9%, and Ringer's Injection.

Diluent Incompatibilities

Lactated Ringer's solution.

Admixture Compatibilities

Physical Compatibility

This list does not constitute an endorsement of the clinical utility or safety of co-administration of Glycopyrrolate Injection with these drugs. Glycopyrrolate Injection is compatible for mixing and injection with the following injectable dosage forms: atropine sulfate, USP; physostigmine salicylate; diphenhydramine HCl; codeine phosphate, USP; benz-quinamide HCl; hydromorphone HCl, USP; droperidol; levorphanol tartrate; lidocaine, USP; meperidine HCl, USP; pyridostigmine bromide; morphine sulfate, USP; nalbuphine HCl; oxymorphone HCl; procaine HCl, USP; promethazine HCl, USP; neostigmine methylsulfate, USP; scopolamine HBr, USP; butorphanol tartrate; fentanyl citrate; trimethobenzamide HCl; and hydroxyzine HCl. Glycopyrrolate Injection may be administered via the tubing of a running infusion of normal saline.

Admixture Incompatibilities

Physical Incompatibility

Because the stability of glycopyrrolate is questionable above a pH of 6.0 do not combine Glycopyrrolate Injection in the same syringe with methohexital Na; chloramphenicol Na succinate; dimenhydrinate; pentobarbital Na; thiopental Na; secobarbital Na; sodium bicarbonate; diazepam; dexamethasone Na phosphate; or pentazocine lactate. These mixtures will result in a pH higher than 6.0 and may result in gas production or precipitation.

2.5 Instructions for Use of Pre-filled Syringe:

Figure 1: Outer Packaging and Prefilled Syringe

1. Inspect the outer packaging (blister pack) to confirm the integrity of the packaging. Do not use if the blister pack or the prefilled syringe has been damaged.
2. Remove the syringe from the outer packaging. (See Figure 2)
  Figure 2
3. Visually inspect the syringe. Parenteral drug products should be inspected visually for particulate matter and discoloration prior to administration, whenever solution and container permit.
4. Twist off the syringe tip cap. Do not remove the label around the luer lock collar. (See Figure 3)
  Figure 3
5. Expel air bubble(s). Adjust the dose (if applicable).
6. Administer the dose ensuring that pressure is maintained on the plunger rod during the entire administration.
7. Discard the used syringe into an appropriate receptacle.

3 DOSAGE FORMS AND STRENGTHS

Glycopyrrolate Injection, USP, is a clear, colorless solution available in 0.6 mg/3 mL (0.2 mg/mL) single-dose, prefilled, disposable syringes.

4 CONTRAINDICATIONS

Glycopyrrolate Injection is contraindicated in:

- patients with known hypersensitivity to Glycopyrrolate Injection or any of its inactive ingredients.
- peptic ulcer patients with the following concurrent conditions: glaucoma; obstructive uropathy (for example, bladder neck obstruction due to prostatic hypertrophy); obstructive disease of the gastrointestinal tract (as in achalasia, pyloroduodenal stenosis, etc.); paralytic ileus, intestinal atony of the elderly or debilitated patient; unstable cardiovascular status in acute hemorrhage; severe ulcerative colitis; toxic megacolon complicating ulcerative colitis; myasthenia gravis.

5 WARNINGS AND PRECAUTIONS

5.1 Precipitation of Acute Glaucoma

Glycopyrrolate Injection may cause mydriasis and increase intraocular pressure in patients with glaucoma. Advise patients with glaucoma to promptly seek medical care in the event that they experience symptoms of acute angle closure glaucoma (pain and reddening of the eyes, accompanied by dilated pupils).

5.2 Drowsiness or Blurred Vision

Glycopyrrolate Injection may cause drowsiness or blurred vision. Warn patients not to participate in activities requiring mental alertness, such as operating a motor vehicle or other machinery, or performing hazardous work, until these issues resolve.

5.3 Heat Prostration

In the presence of fever, high environmental temperature, and/or during physical exercise, heat prostration can occur with use of anticholinergic agents including Glycopyrrolate Injection (due to decreased sweating), particularly in children and the elderly. Advise patients to avoid exertion and high environmental temperature after receiving Glycopyrrolate Injection.

5.4 Intestinal Obstruction

Diarrhea may be an early symptom of incomplete intestinal obstruction, especially in patients with ileostomy or colostomy. In this instance treatment with Glycopyrrolate Injection is inappropriate and possibly harmful. Avoid use in patients with these conditions.

5.5 Tachycardia

Investigate any tachycardia before giving Glycopyrrolate Injection because an increase in the heart rate may occur. Use with caution in patients with coronary artery disease, congestive heart failure, cardiac arrhythmias, hypertension, and/or hyperthyroidism.

5.6 Risk of Use in Patients with Renal Impairment

Renal elimination of glycopyrrolate may be severely impaired in patients with renal failure. Dosage adjustments may be necessary in this population [see Pharmacokinetics (12.3)]

5.7 Autonomic Neuropathy, Hepatic Disease, Ulcerative Colitis, Prostatic Hypertrophy, or Hiatal Hernia

Use Glycopyrrolate Injection with caution in the elderly and in all patients with autonomic neuropathy, hepatic disease, ulcerative colitis, prostatic hypertrophy, or hiatal hernia, because anticholinergic drugs may aggravate these conditions. Consider dose reduction and closely monitor the elderly and patients with autonomic neuropathy, hepatic disease, ulcerative colitis, prostatic hypertrophy, or hiatal hernia.

5.8 Delayed Gastric Emptying/Gastric Stasis

The use of anticholinergetic drugs, including Glycopyrrolate Injection, in the treatment of gastric ulcer may produce a delay in gastric emptying due to antral statis. Monitor patients for symptoms such as vomiting, dyspepsia, early satiety, abdominal distention, and increased abdominal pain. Discontinue Glycopyrrolate Injection treatment if these symptoms develop or worsen on treatment.

5.9 Light Sensitivity

Patients may experience sensitivity of the eyes to light. Advise patients to protect their eyes from light after receiving Glycopyrrolate Injection.

6 ADVERSE REACTIONS

The following adverse reactions were identified in clinical studies or postmarketing reports. Because some of these reactions were reported voluntarily from a population of uncertain size, it is not always possible to reliably estimate their frequency or establish a causal relationship to drug exposure.

Adverse reactions to anticholinergics include xerostomia (dry mouth); urinary hesitancy and retention; blurred vision and photophobia due to mydriasis (dilation of the pupil); cycloplegia; increased ocular tension; tachycardia; palpitation; decreased sweating; loss of taste; headache; nervousness; drowsiness; weakness; dizziness; insomnia; nausea; vomiting; impotence; suppression of lactation; constipation; bloated feeling; severe allergic reactions including anaphylactic/anaphylactoid reactions; hypersensitivity; urticaria, pruritus, dry skin, and other dermal manifestations; some degree of mental confusion and/or excitement, especially in elderly persons.

The following adverse events have been reported from post-marketing experience with glycopyrrolate: malignant hyperthermia; cardiac arrhythmias (including bradycardia, ventricular tachycardia, ventricular fibrillation); cardiac arrest; hypertension; hypotension; seizures; and respiratory arrest. Post-marketing reports have included cases of heart block and QTc interval prolongation associated with the combined use of glycopyrrolate and an anticholinesterase. Injection site reactions including pruritus, edema, erythema, and pain have also been reported.

7 DRUG INTERACTIONS

The concurrent use of Glycopyrrolate Injection with other anticholinergics or medications with anticholinergic activity, such as phenothiazines, antiparkinson drugs, or tricyclic antidepressants, may intensify the antimuscarinic effects and result in an increase in anticholinergic side effects.

Concomitant administration of Glycopyrrolate Injection and potassium chloride in a wax matrix may increase the severity of potassium chloride-induced gastrointestinal lesions as a result of a slower gastrointestinal transit time.

8 USE IN SPECIFIC POPULATIONS

8.1 Pregnancy

Risk summary

Limited data are available with glycopyrrolate use during pregnancy have not identified a drug-associated risk of birth defects and miscarriage, however, most of the reported exposures occurred after the first trimester. Most of the available data are based on studies with exposures that occurred at the time of Cesarean-section delivery, and these studies have not identified an adverse effect on maternal outcomes or infant Apgar scores (see Data).

In animal reproduction studies in pregnant rats and rabbits administered glycopyrrolate orally (rats) and intramuscularly (rabbits) during the period of organogenesis, no teratogenic effects were seen at 320-times and 5 times the maximum recommended human dose (MRHD) of 2 mg (on a mg/m^2 basis), respectively (see Data).

The estimated background risk for major birth defects and miscarriage for the indicated population is unknown. All pregnancies have a background risk of birth defect, loss, or other adverse outcomes. In the U.S. general population, the estimated background risk of major birth defects and miscarriage in the clinically recognized pregnancies is 2-4% and 15−20%, respectively.

Data

Human Data

Published, randomized, controlled trials over several decades, which compared the use of glycopyrrolate to another antimuscarinic agent in pregnant women during Cesarean section, have not identified adverse maternal or infant outcomes. In normal doses (0.004 mg/kg), glycopyrrolate does not appear to affect fetal heart rate or fetal heart rate variability to a significant degree. Concentrations of glycopyrrolate in umbilical venous and arterial blood and in the amniotic fluid are low after intramuscular administration to parturients. Therefore, glycopyrrolate does not appear to penetrate through the placental barrier in significant amounts.

There are no studies on the safety of glycopyrrolate exposure during the period of organogenesis, and therefore, it is not possible to draw any conclusions on the risk of birth defects following exposure to glycopyrrolate during pregnancy. In addition, there are no data on the risk of miscarriage following fetal exposure to glycopyrrolate.

Animal Data

Reproduction studies with glycopyrrolate were performed in rats at a dietary dose of approximately 65 mg/kg/day (exposure was approximately 320 times the maximum recommended daily human dose of 2 mg on a mg/m^2 basis) and rabbits at intramuscular doses of up to 0.5 mg/kg/day (exposure was approximately 5 times the maximum recommended daily human dose on a mg/m^2 basis). These studies produced no teratogenic effects to the fetus.

A preclinical study on reproductive performance of rats given glycopyrrolate resulted in a decreased rate of conception and survival at weaning.

8.2 Lactation

Risk summary

There are no data on the presence of glycopyrrolate in either human milk or animal milk, the effects on the breastfed infant, or the effects on milk production. As with other anticholinergics, glycopyrrolate may cause suppression of lactation [see Adverse Reactions (6)]. The developmental and health benefits of breast feeding should be considered along with the mother's clinical need for Glycopyrrolate Injection and any potential adverse effects on the breastfed child from Glycopyrrolate Injection or from the underlying maternal condition.

8.4 Pediatric Use

Safety and effectiveness in pediatric patients have not been established for the management of peptic ulcer.

Dysrhythmias associated with the use of glycopyrrolate intravenously as a premedicant or during anesthesia have been observed in pediatric patients.

Infants, patients with Down's syndrome, and pediatric patients with spastic paralysis or brain damage may experience an increased response to anticholinergics, thus increasing the potential for side effects.

A paradoxical reaction characterized by hyperexcitability may occur in pediatric patients taking large doses of anticholinergics including Glycopyrrolate Injection. Infants and young children are especially susceptible to the toxic effects of anticholinergics.

8.5 Geriatric Use

Clinical Studies of Glycopyrrolate Injection did not include sufficient numbers of subjects aged 65 and over to determine whether they respond differently from younger subjects. Other reported clinical experience has not identified differences in responses between the elderly and younger patients. In general, dose selection for an elderly patient should be cautious, usually starting at the low end of the dosing range, reflecting the greater frequency of decreased hepatic, renal, or cardiac function, and of concomitant disease or other therapy.

8.6 Renal Impairment

Renal elimination of glycopyrrolate may be severely impaired in patients with renal failure. Dosage adjustments may be necessary [see Clinical Pharmacology (12.3)].

10 OVERDOSAGE

To combat peripheral anticholinergic effects, a quaternary ammonium anticholinesterase such as neostigmine methylsulfate (which does not cross the blood-brain barrier) may be given intravenously in increments of 0.25 mg in adults. This dosage may be repeated every five to ten minutes until anticholinergic overactivity is reversed or up to a maximum of 2.5 mg. Proportionately smaller doses should be used in pediatric patients. Indication for repetitive doses of neostigmine should be based on close monitoring of the decrease in heart rate and the return of bowel sounds.

If CNS symptoms (e.g., excitement, restlessness, convulsions, psychotic behavior) occur, physostigmine (which does cross the blood–brain barrier) may be used. Physostigmine 0.5 to 2 mg should be slowly administered intravenously and repeated as necessary up to a total of 5 mg in adults. Proportionately smaller doses should be used in pediatric patients.

To combat hypotension, administer IV fluids and/or pressor agents along with supportive care.

Fever should be treated symptomatically.

Following overdosage, a curare-like action may occur, i.e., neuromuscular blockade leading to muscular weakness and possible paralysis. In the event of a curare-like effect on respiratory muscles, artificial respiration should be instituted and maintained until effective respiratory action returns.

11 DESCRIPTION

Glycopyrrolate Injection, USP is a synthetic anticholinergic agent. It is intended for intramuscular or intravenous administration. Each 1 mL contains:

Glycopyrrolate, USP 0.2 mg, Water for Injection, USP q.s., pH adjusted, when necessary, with hydrochloric acid and/or sodium hydroxide. Solution does not contain preservatives.

Glycopyrrolate is a quaternary ammonium salt with the following chemical name:

3[(cyclopentylhydroxyphenylacetyl)oxy]-1,1-dimethyl pyrrolidinium bromide.

Its structural formula is as follows:

Glycopyrrolate occurs as a white, odorless crystalline powder. It is soluble in water and alcohol, and practically insoluble in chloroform and ether. It completely ionized at physiological pH values. Glycopyrrolate Injection, USP, is a clear, colorless, sterile liquid; pH 2.0 to 3.0. The partition coefficient of glycopyrrolate in a n-octanol/water system is 0.304 (log10 P= -1.52) at ambient room temperature (24°C).

12 CLINICAL PHARMACOLOGY

12.1 Mechanism of Action

Glycopyrrolate, like other anticholinergic (antimuscarinic) agents, inhibits the action of acetylcholine on structures innervated by postganglionic cholinergic nerves and on smooth muscles that respond to acetylcholine but lack cholinergic innervation. These peripheral cholinergic receptors are present in the autonomic effector cells of smooth muscle, cardiac muscle, the sinoatrial node, the atrioventricular node, exocrine glands and, to a limited degree, in the autonomic ganglia. Thus, it diminishes the volume and free acidity of gastric secretions and controls excessive pharyngeal, tracheal, and bronchial secretions.

12.2 Pharmacodynamics

Glycopyrrolate antagonizes muscarinic symptoms (e.g., bronchorrhea, bronchospasm, bradycardia, and intestinal hypermotility) induced by cholinergic drugs such as the anticholinesterases. The highly polar quaternary ammonium group of glycopyrrolate limits its passage across lipid membranes, such as the blood-brain barrier, in contrast to atropine sulfate and scopolamine hydrobromide, which are highly non-polar tertiary amines which penetrate lipid barriers easily. For this reason, the occurrence of CNS-related side effects is lower, in comparison to their incidence following administration of anticholinergics which are chemically tertiary amines that can cross this barrier readily. With intravenous injection, the onset of action is generally evident within one minute. Following intramuscular administration, the onset of action is noted in 15 to 30 minutes, with peak effects occurring within approximately 30 to 45 minutes. The vagal blocking effects persist for 2 to 3 hours and the antisialagogue effects persist up to 7 hours, periods longer than for atropine.

12.3 Pharmacokinetics

The following pharmacokinetic information and conclusions were obtained from published studies that used nonspecific assay methods.

Distribution

The mean volume of distribution of glycopyrrolate was estimated to be 0.42 ± 0.22 L/kg.

Elimination

Metabolism

The in vivo metabolism of glycopyrrolate in humans has not been studied.

Excretion

The mean clearance and mean t1/2 values were reported to be 0.54 ± 0.14 L/kg/hr and 0.83 ± 0.27 hr, respectively post IV administration. After IV administration of a 0.2 mg radiolabeled glycopyrrolate, 85% of dose recovered was recovered in urine 48 hours postdose and some of the radioactivity was also recovered in bile. After IM administration of glycopyrrolate to adults, the mean t1/2 value is reported to be between 0.55 to 1.25 hrs. Over 80% of IM dose administered was recovered in urine and the bile as unchanged drug and half the IM dose is excreted within 3 hrs. The following table summarizes the mean and standard deviation of pharmacokinetic parameters from a study.

Group | t1/2 (hr) | Vss (L/kg) | CL (L/kg/hr) | Tmax (min) | Cmax (mcg /L) | AUC (mcg/L●hr)
(6 mcg/kg IV) | 0.83 ± 0.27 | 0.42 ± 0.22 | 0.54 ± 0.14 | - | - | 8.64 ± 1.49*
(8 mcg/kg IM) | - | - | - | 27.48 ± 6.12 | 3.47 ± 1.48 | 6.64 ± 2.33*
* 0 to 8 hr

Specific Populations

Pediatric Patients

Following IV administration (5 mcg/kg glycopyrrolate) to infants and children, the mean t1/2 values were reported to be between 21.6 and 130.0 minutes and between 19.2 and 99.2 minutes, respectively.

Patients with Renal Impairment

In one study glycopyrrolate was administered IV in uremic patients undergoing renal transplantation. The mean elimination half-life was significantly longer (46.8 minutes) than in healthy patients (18.6 minutes). The mean area-under-the-concentration-time curve (10.6 hr- mcg /L), mean plasma clearance (0.43 L/hr/kg), and mean 3-hour urine excretion (0.7%) for glycopyrrolate were also significantly different than those of controls (3.73 hr-mcg/L, 1.14 L/hr/kg, and 50%, respectively). These results suggest that the elimination of glycopyrrolate is severely impaired in patients with renal failure.

13 NONCLINICAL TOXICOLOGY

Carcinogenesis

Long-term studies in animals have not been performed to evaluate carcinogenic potential.

Mutagenesis

Studies to evaluate the mutagenic potential of glycopyrrolate have not been conducted.

Impairment of Fertility

In reproduction studies in rats, dietary administration of glycopyrrolate resulted in diminished rates of conception in a dose-related manner. Other studies in dogs suggest that this may be due to diminished seminal secretion which is evident at high doses of glycopyrrolate.

16 HOW SUPPLIED/STORAGE AND HANDLING

Glycopyrrolate Injection, USP, 0.2 mg per mL without preservative is available as:

Product Code | Unit of Sale | Strength | Each
720330 | NDC 76045-023-30 Unit of 10 | 0.6 mg/3 mL (0.2 mg/mL) | NDC 76045-023-00 3 mL single-dose pre-filled disposable syringe
RF720330 | NDC 76045-223-30 Unit of 10 | 0.6 mg/3 mL (0.2 mg/mL) | NDC 76045-223-03 3 mL single-dose pre-filled disposable syringe This product contains an RFID.

Store at 20° to 25°C (68° to 77°F) [See USP Controlled Room Temperature.]

Sensitive to heat – Do not autoclave. Discard unused portion.

Do not place syringe on a sterile field.

17 PATIENT COUNSELING INFORMATION

Drowsiness or Blurred Vision: Inform patients that Glycopyrrolate Injection may cause drowsiness or blurred vision. Warn patients not to operate a motor vehicle or other machinery or perform hazardous work until these issues resolve. [see Warnings and Precautions (5.2)].

Heat Prostration: Inform patients that in the presence of fever, high environmental temperature and/or during physical exercise, heat prostration can occur with use of anticholinergic agents, including Glycopyrrolate Injection (due to decreased sweating), particularly in children and the elderly. Advise patients to avoid exertion and high environmental temperature after receiving Glycopyrrolate Injection [see Warnings and Precautions (5.3)].

Light Sensitivity: Advise patients that Glycopyrrolate Injection may cause sensitivity of the eyes to light and to protect their eyes from light after receiving Glycopyrrolate Injection [see Warnings and Precautions (5.9)].

Drug Interactions: Inform patients that Glycopyrrolate Injection may interact with other drugs. Advise patients to report to their healthcare provider the use of any other medication [see Drug Interactions (7)].

For more information concerning this drug, please call Fresenius Kabi USA, LLC at 1-800-551-7176.

To report SUSPECTED ADVERSE REACTIONS, contact Fresenius Kabi USA, LLC at 1-800-551-7176 or FDA at 1-800-FDA-1088 or www.fda.gov/medwatch.

U.S. Patent 9,731,082

www.fresenius-kabi.com/us

451718D

PACKAGE LABEL

PACKAGE LABEL - PRINCIPAL DISPLAY – Glycopyrrolate Injection, USP 3 mL Syringe Label

3 mL Single-Dose Prefilled Syringe. For IM or IV Use. Rx only

Glycopyrrolate Injection, USP

0.6 mg / 3 mL (0.2 mg /mL)

PACKAGE LABEL

PACKAGE LABEL - PRINCIPAL DISPLAY – Glycopyrrolate Injection, USP 3 mL Blister Label

RF720330 NDC 76045-223-03

Glycopyrrolate Injection, USP

0.6 mg / 3 mL (0.2 mg /mL)

For Intramuscular or Intravenous Use. Rx only

PACKAGE LABEL

PACKAGE LABEL - PRINCIPAL DISPLAY – Glycopyrrolate Injection, USP 3 mL Carton Label

Rx only NDC 76045-223-30

Glycopyrrolate Injection, USP

0.6 mg / 3 mL (0.2 mg /mL)

For Intramuscular or Intravenous Use.

Do NOT place syringe on a Sterile Field.

10 x 3 ml Single-Dose Prefilled Syringes

Discard unused portion.

PACKAGE LABEL

PACKAGE LABEL - PRINCIPAL DISPLAY – Glycopyrrolate Injection, USP 3 mL Blister Label

Rx only NDC 76045-023-00

Glycopyrrolate Injection, USP

0.6 mg / 3 mL (0.2 mg /mL)

For Intramuscular or Intravenous Use.

PACKAGE LABEL

PACKAGE LABEL - PRINCIPAL DISPLAY – Glycopyrrolate Injection, USP 3 mL Carton Label

Rx only NDC 76045-023-30

Glycopyrrolate Injection, USP

0.6 mg / 3 mL (0.2 mg /mL)

For Intramuscular or Intravenous Use.

Do NOT place syringe on a Sterile Field.

10 x 3 ml Single-Dose Prefilled Syringes

Discard unused portion.